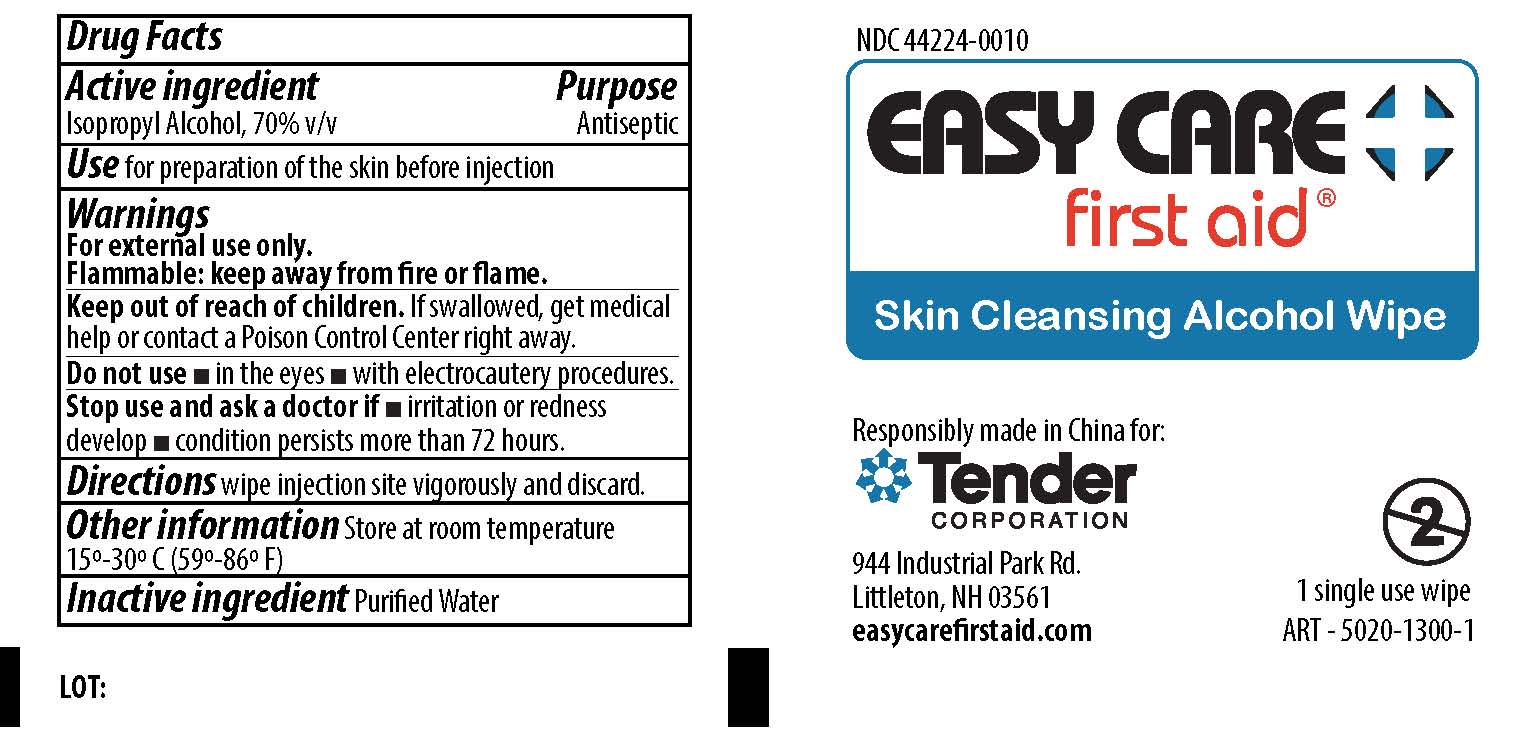 DRUG LABEL: Easy Care First Aid Skin Cleansing Alcohol Wipe
NDC: 44224-0010 | Form: SWAB
Manufacturer: Tender Corporation
Category: otc | Type: HUMAN OTC DRUG LABEL
Date: 20190930

ACTIVE INGREDIENTS: ISOPROPYL ALCOHOL 70 mL/100 mL
INACTIVE INGREDIENTS: WATER

Easy Care Skin Cleansing Alcohol wipe

Active Ingredient

Isopropyl Alcohol, 70% v/v

Purpose

Antiseptic

Use

For preparation of skin before injection.

Warnings

For external use only.

Flammable - keep away from fire or flame

Keep out of reach of children.

If swallowed, get medical help or contact a Poison Control Center right away.

Do not use

- in the eyes
- with electrocautery procedures

Stop use and ask a doctor if

- irritation and redness develop
- condition persists for more than 72 hours

Other information

Store at room temperature 15-30 degree Celsius (59-86 degree Fahrenheit)

Directions

Wipe Injection site vigorously and discard.

Inactive Ingredient

Purified water.

PACKAGE LABEL

Easy Care First Aid® Skin Cleansing Alcohol Wipe

Responsibly made in China for:

Tender Corporation

944 Industrial Park Rd.

Littleton, NH 03561
easycarefirstaid.com

1 single use wipe